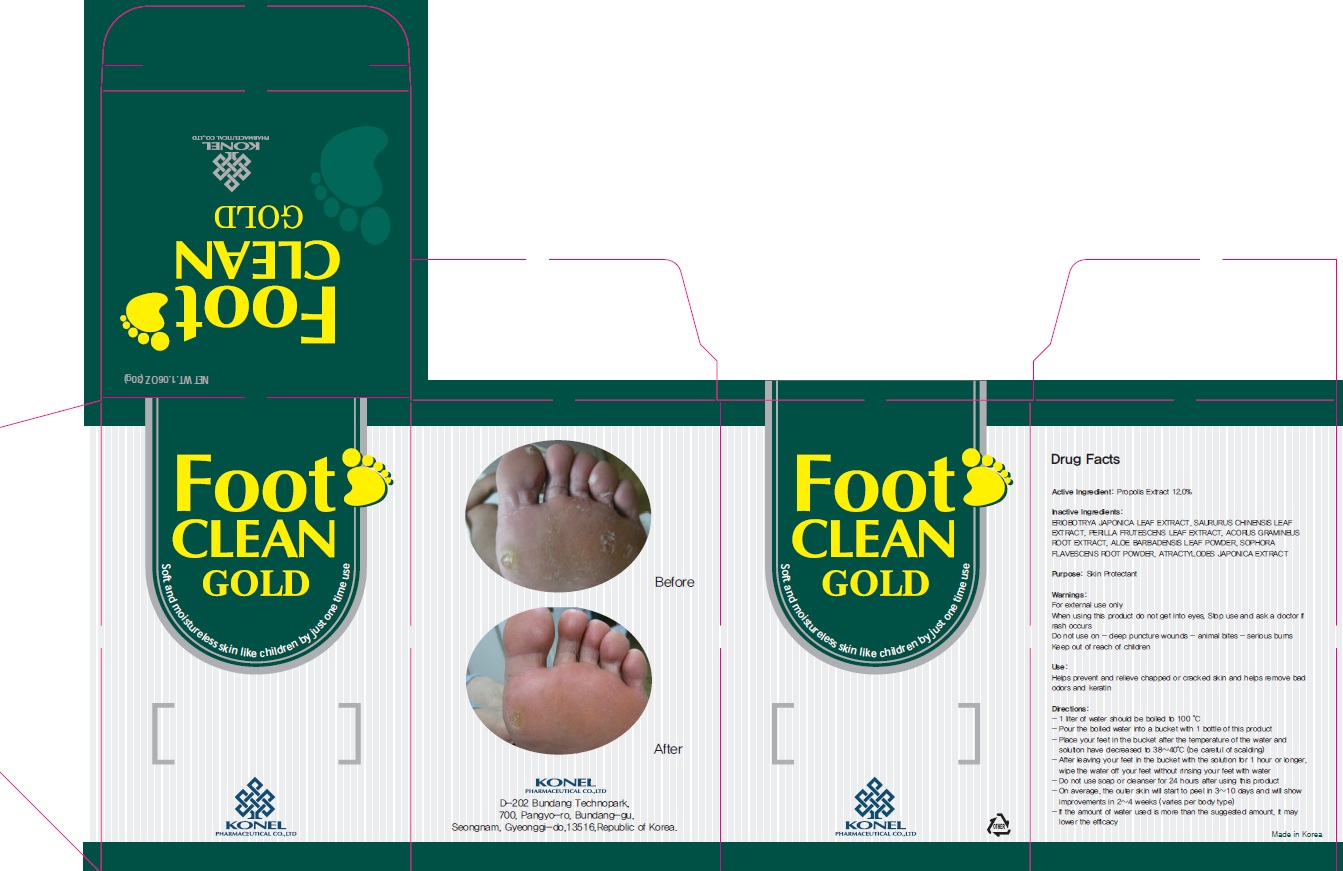 DRUG LABEL: Foot Clean Gold
NDC: 71059-010 | Form: POWDER
Manufacturer: KONEL
Category: otc | Type: HUMAN OTC DRUG LABEL
Date: 20221027

ACTIVE INGREDIENTS: PROPOLIS WAX 3.6 g/30 g
INACTIVE INGREDIENTS: ERIOBOTRYA JAPONICA LEAF; PERILLA FRUTESCENS LEAF

ACTIVE INGREDIENT

Active Ingredient: Propolis Extract 12.0%

INACTIVE INGREDIENT

Inactive Ingredients: ERIOBOTRYA JAPONICA LEAF EXTRACT, SAURURUS CHINENSIS LEAF EXTRACT, PERILLA FRUTESCENS LEAF EXTRACT, ACORUS GRAMINEUS ROOT EXTRACT, ALOE BARBADENSIS LEAF POWDER, SOPHORA FLAVESCENS ROOT POWDER, ATRACTYLODES JAPONICA EXTRACT

PURPOSE

Purpose: Skin Protectant

WARNINGS

Warnings: For external use only When using this product do not get into eyes, Stop use and ask a doctor if rash occurs Do not use on - deep puncture wounds - animal bites - serious burns Keep out of reach of children

KEEP OUT OF REACH OF CHILDREN

Use

Use: Helps prevent and relieve chapped or cracked skin and helps remove bad odors and keratin

Directions

Directions: - 1 liter of water should be boiled to 100 °C - Pour the boiled water into a bucket with 1 bottle of this product - Place your feet in the bucket after the temperature of the water and solution have decreased to 38~40°C (be careful of scalding) - After leaving your feet in the bucket with the solution for 1 hour or longer, wipe the water off your feet without rinsing your feet with water - Do not use soap or cleanser for 24 hours after using this product - On average, the outer skin will start to peel in 3~10 days and will show improvements in 2~4 weeks (varies per body type) - If the amount of water used is more than the suggested amount, it may lower the efficacy